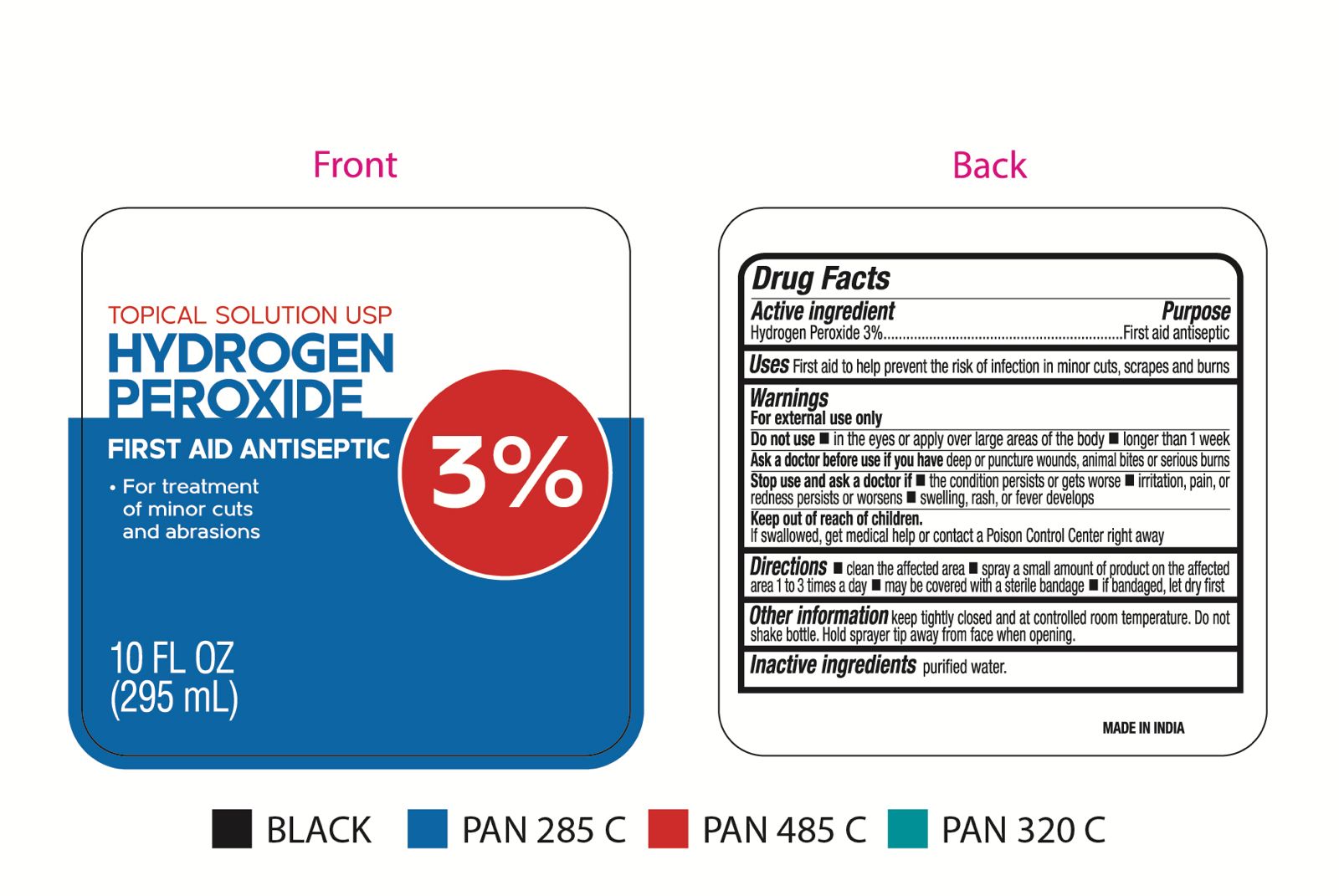 DRUG LABEL: 3 Hydrogen Peroxide
NDC: 30400-250 | Form: LIQUID
Manufacturer: Jell Pharmaceuticals Pvt Ltd.
Category: otc | Type: HUMAN OTC DRUG LABEL
Date: 20250924

ACTIVE INGREDIENTS: HYDROGEN PEROXIDE 30 mg/1 mL
INACTIVE INGREDIENTS: WATER

3% Hydrogen Peroxide Spray

Active ingredient

Hydrogen Peroxide 3%

Purpose

First aid antiseptic

Uses

First aid to help prevent the risk of infection in minor cuts, scrapes and burns

Warnings

For external use only

Do not use

- in the eyes or apply over large areas of the body
- longer than 1 week.

Ask a doctor before use if you have

deep or puncture wounds, animals bites or serious burns

Stop use and ask a doctor if

- the condition persists or gets worse
- irritation, pain, or redness persists or worsens
- swelling, rash, or fever develops

Keep out of reach of children.

Is swallowed, get medical help or contact a Poison Control Center right away

Directions

- clean the affected area
- spray a small amount of product on the affected area 1 to 3 times a day
- may be covered with a sterile bandage
- if bandaged, let dry first

Other information

keep tightly closed and at controlled room temperature. Do not shake bottle. Hold srayer tip away from face when opening.

Inactive ingredients

purified water